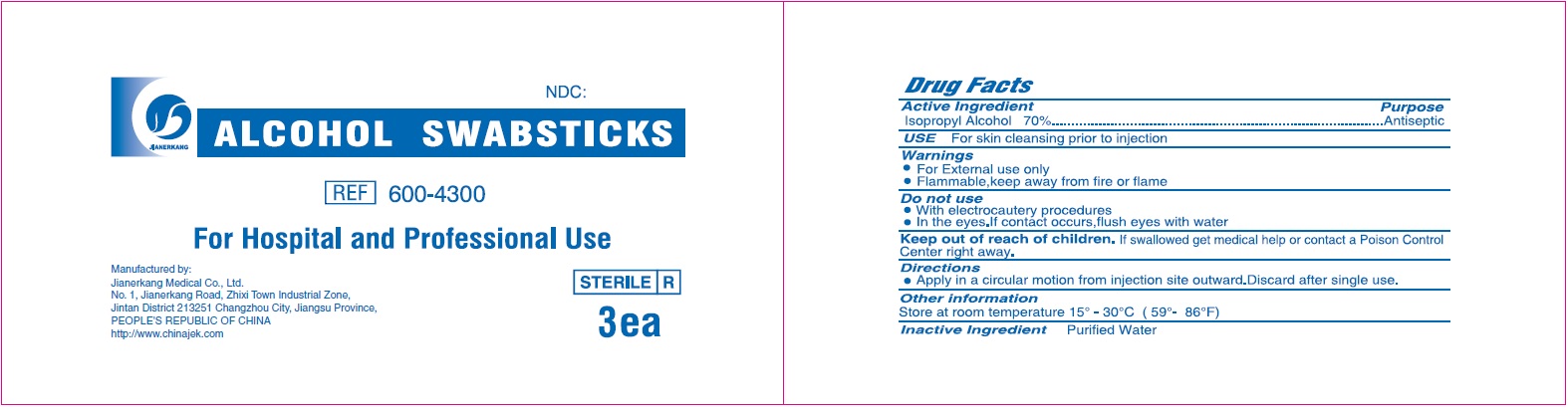 DRUG LABEL: Alcohol Swabsticks 3s Sterile
NDC: 34645-0020 | Form: SWAB
Manufacturer: Jianerkang Medical Co., Ltd
Category: otc | Type: HUMAN OTC DRUG LABEL
Date: 20231023

ACTIVE INGREDIENTS: ISOPROPYL ALCOHOL 0.7 mL/1 mL
INACTIVE INGREDIENTS: WATER

ALCOHOL SWABSTICKS 3's Sterile

Active Ingredient

Isopropyl Alcohol 70%

Purpose

Antiseptic

USE

For skin cleansing prior to injection

Warnings

- For External ues only
- Flammable,keep away from fire or flame

Do not use

- With electrocautery procedures
- In the eyes.If contact occurs, flush eyes with water

Keep out of reach of children.

If swallowed get medical help or contact a Poison Control Center right away.

Directions

- Apply in a circular motion from injection site outward.Discard after single use.

Other information

Store at room temperature 15° - 30°C (59° 86°F)

Inactive Ingredient

Purified Water